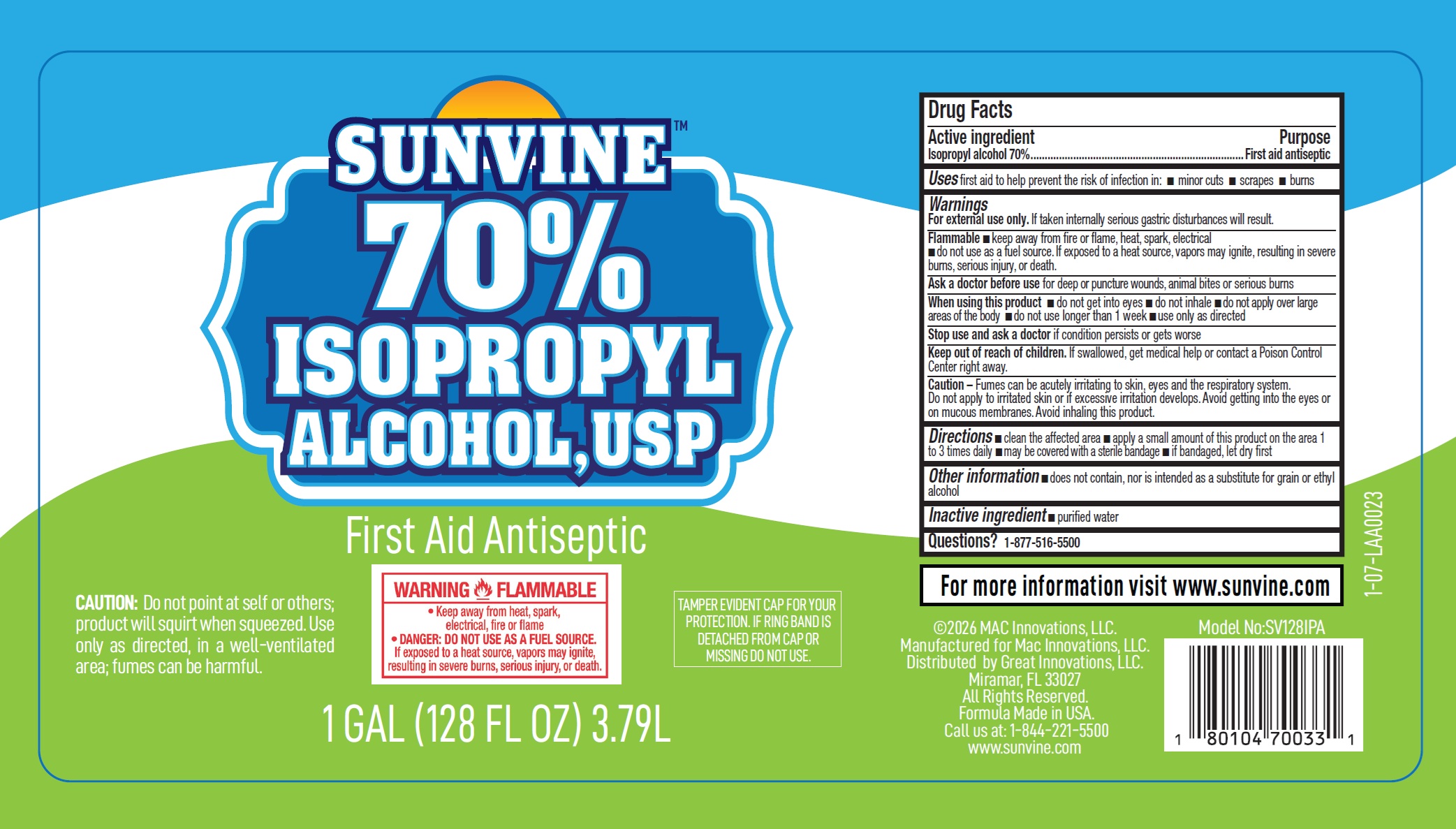 DRUG LABEL: Sunvine 70 Isopropyl Alcohol First Aid Antiseptic
NDC: 81790-002 | Form: LIQUID
Manufacturer: Mac Innovations, LLC
Category: otc | Type: HUMAN OTC DRUG LABEL
Date: 20260224

ACTIVE INGREDIENTS: ISOPROPYL ALCOHOL 70 mL/100 mL
INACTIVE INGREDIENTS: WATER

Sunvine 70% Isopropyl Alcohol First Aid Antiseptic

Active ingredient

Isopropyl alcohol 70%

Purpose

First aid antiseptic

Uses

first aid to help prevent the risk of infection in:

- minor cuts
- scrapes
- burns

Warnings

For external useonly. If taken internally serious gastric disturbances will result.

Flammable

- keep away from fire or flame, heat, spark, electrical
- do not use as a fuel source. If exposed to a heat source, vapors may ignite, resulting in severe burns, serious injury, or death.

Ask a doctor before use

for deep or puncture wounds, animal bites or serious burns

When using this product

- do not get into eyes
- do not inhale
- do not apply over large areas of the body
- do not use longer than 1 week
- use only as directed

Stop use and ask a doctor

if condition persists or gets worse

Keep out of reach of children.

If swallowed, get medical help or contact a Poison Control Center right away.

Caution– Fumes can be acutely irritating to skin, eyes and the respiratory system.
Do not apply to irritated skin or if excessive irritation develops. Avoid getting into the eyes or
on mucous membranes. Avoid inhaling this product.

Directions

- clean the affected area
- apply a small amount of this product on the area 1 to 3 times daily
- may be covered with a sterile bandage
- if bandaged, let dry first

Other information

- does not contain, nor is intended as a substitute for grain or ethyl alcohol

Inactive ingredient

- purified water

Questions?

1-877-516-5500